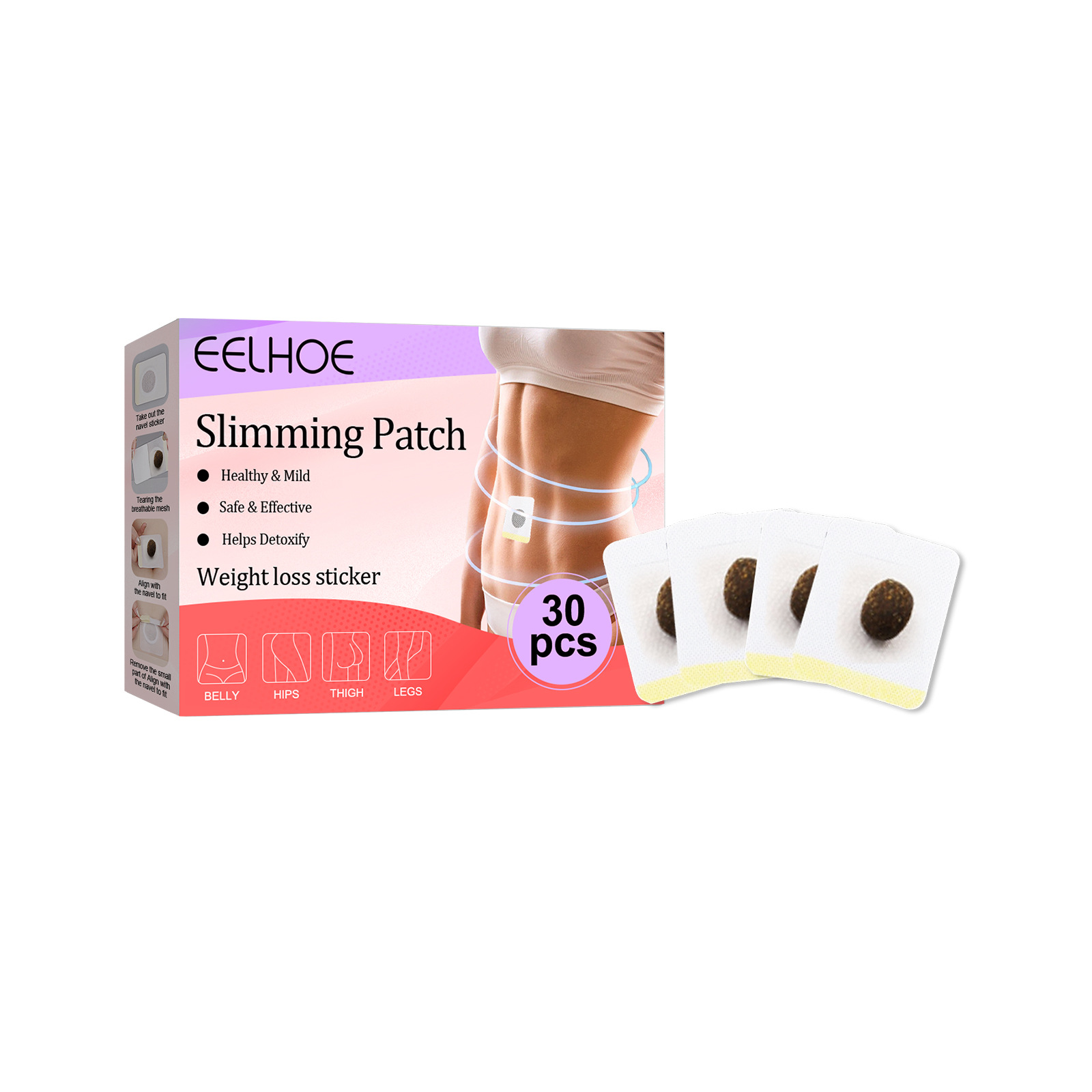 DRUG LABEL: Slimming Patch
NDC: 83675-028 | Form: PATCH
Manufacturer: Guangzhou Hanhai Trading Co., Ltd
Category: otc | Type: HUMAN OTC DRUG LABEL
Date: 20231008

ACTIVE INGREDIENTS: COFFEE BEAN 23 g/100 1
INACTIVE INGREDIENTS: NELUMBO NUCIFERA LEAF; MINT; HAWTHORN LEAF WITH FLOWER

Active Ingredient

Coffee Bean 23.0%

Purpose

Slimming

Use

Eliminate edema
Tighten the arm
Slender and smooth

Warnings

For external use only. Do not take it internally.

Keep Out Of Reach Of Children
Sensitive Skin

Do not use

Product shall not be eat

When Using

1.Take out the navel sticker
2.Tearing the breathable mesh
3.Align with the navel to fit
4.Remove the smallpart of Align withthe navel to fit

Stop Use

In case of adverse reactions, please stop using this product.If the symptoms.

Ask Doctor

ask doctor in case of Sensitive Skin

Keep Oot Of Reach Of Children

Keep Out Of Reach Of Children

Directions

1.Take out the navel sticker
2.Tearing the breathable mesh
3.Align with the navel to fit
4.Remove the smallpart of Align withthe navel to fit

Other information

Store the product in a cool, dry and well-ventilated place

Avoid direct sunlight

Inactive ingredients

Hawthorn
Lotus Leaf

Mint